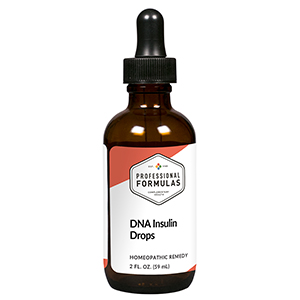 DRUG LABEL: DNA Insulin Drops
NDC: 63083-2019 | Form: LIQUID
Manufacturer: Professional Complementary Health Formulas
Category: homeopathic | Type: HUMAN OTC DRUG LABEL
Date: 20190815

ACTIVE INGREDIENTS: CHROMIUM 6 [hp_X]/59 mL; LYCOPODIUM CLAVATUM SPORE 6 [hp_X]/59 mL; VANADIUM 6 [hp_X]/59 mL; PANCRELIPASE AMYLASE 6 [hp_X]/59 mL; INSULIN GLULISINE 12 [hp_X]/59 mL; PHOSPHORIC ACID 30 [hp_X]/59 mL; URANYL NITRATE HEXAHYDRATE 30 [hp_X]/59 mL; RADIUM BROMIDE 60 [hp_X]/59 mL
INACTIVE INGREDIENTS: ALCOHOL; WATER

C19

ACTIVE INGREDIENTS

Chromium muriaticum 6X
Lycopodium clavatum 6X
Vanadium metallicum 6X
Pancreatinum 6X, 12X, 30X, 100X
DNA insulin 12X, 60X, 100X, 1000X
Phosphoricum acidum 30X
Uranium nitricum 30X
Radium bromatum 60X

QUESTIONS

Professional Formulas

PO Box 2034 Lake Oswego, OR 97035

INDICATIONS

For the temporary relief of increased hunger or thirst, frequent urination, fatigue, nausea, or vomiting.*

PURPOSE

*Claims based on traditional homeopathic practice, not accepted medical evidence. Not FDA evaluated.

WARNINGS

Consult a doctor if condition worsens or if symptoms persist. Keep out of the reach of children. In case of overdose, get medical help or contact a poison control center right away. If pregnant or breastfeeding, ask a healthcare professional before use.

Keep out of the reach of children.

PREGNANCY OR BREAST FEEDING

If pregnant or breastfeeding, ask a healthcare professional before use.

DIRECTIONS

Place drops under tongue 30 minutes before/after meals. Adults and children 12 years and over: Take 10 drops up to 3 times per day. Consult a physician for use in children under 12 years of age.

OTHER INFORMATION

Tamper resistant. If seal is broken, do not use. After opening, close container tightly and store at room temperature away from heat.

INACTIVE INGREDIENTS

20% ethanol, purified water.

LABEL

Est 1985

Professional Formulas

Complementary Health

DNA Insulin Drops

Homeopathic Remedy

2 FL. OZ. (59 mL)